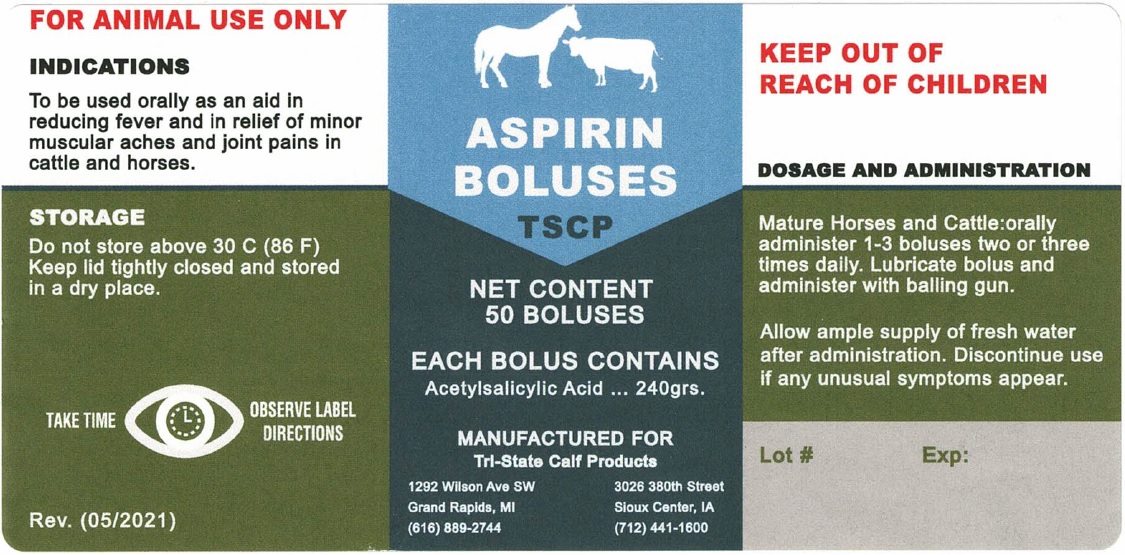 DRUG LABEL: Aspirin Bolus
NDC: 86159-101 | Form: TABLET
Manufacturer: Tri-State Calf Products, Inc.
Category: animal | Type: OTC ANIMAL DRUG LABEL
Date: 20220406

ACTIVE INGREDIENTS: ASPIRIN 16 g/1 1
INACTIVE INGREDIENTS: STARCH, CORN

TSCP ASPIRIN BOLUSES

EACH BOLUS CONTAINS:

Acetylsalicylic Acid.....240grs.

KEEP OUT OF REACH OF CHILDREN

DOSAGE AND ADMINISTRATION

Mature Horses and Cattle: orally administer 1-3 boluses two or three times daily. Lubricate bolus and administer with balling gun.

Allow ample supply of fresh water after administration. Discontinue use if any unusual symptoms appear.

INDICATIONS

To be used orally as an aid in reducing fever and in relief of minor muscular aches and joint pains in cattle and horses.

STORAGE

Do not store above 30 C (86 F)
Keep lid tightly closed and stored in a dry place.

TSCP

FOR ANIMAL USE ONLY

TAKE TIME OBSERVE LABEL DIRECTIONS

MANUFACTURED FOR
Tri-State Calf Products

1292 Wilson Ave SW 3026 380th Street
Grand Rapids, MI Sioux Center, IA
(616) 889-2744 (712) 441-1600